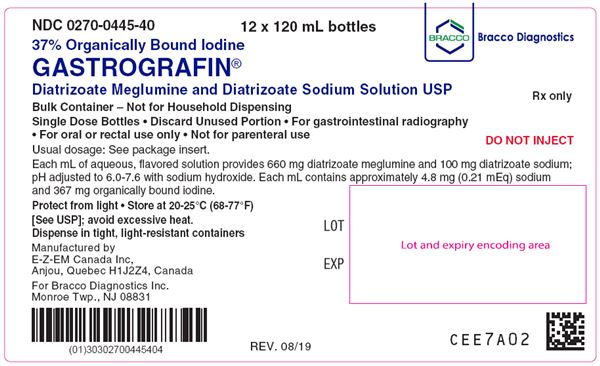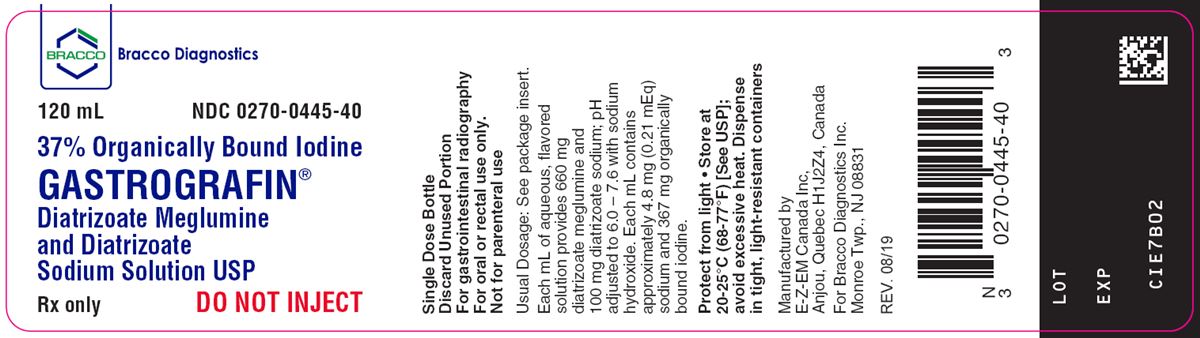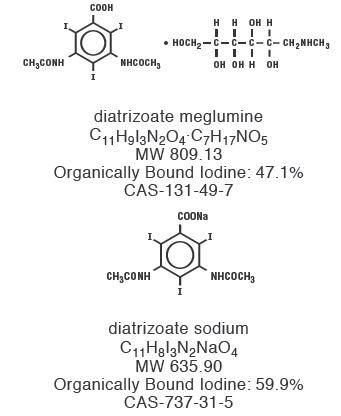 DRUG LABEL: Gastrografin
NDC: 0270-0445 | Form: LIQUID
Manufacturer: Bracco Diagnostics Inc
Category: prescription | Type: HUMAN PRESCRIPTION DRUG LABEL
Date: 20211004

ACTIVE INGREDIENTS: diatrizoate meglumine 660 mg/1 mL; diatrizoate sodium 100 mg/1 mL
INACTIVE INGREDIENTS: SODIUM CITRATE 3.22 mg/1 mL; EDETATE DISODIUM 0.403 mg/1 mL; SACCHARIN SODIUM 2.77 mg/1 mL

GASTROGRAFIN®
Diatrizoate Meglumine
and Diatrizoate Sodium
Solution USP

DESCRIPTION

Gastrografin (Diatrizoate Meglumine and Diatrizoate Sodium Solution) is a palatable lemon-flavored water-soluble iodinated radiopaque contrast medium for oral or rectal administration only. Each mL contains 660 mg diatrizoate meglumine and 100 mg diatrizoate sodium; pH has been adjusted to 6.0 to 7.6 with sodium hydroxide. Each mL contains approximately 4.8 mg (0.21 mEq) sodium and 367 mg organically bound iodine. Inactive ingredients: edetate disodium, flavor, polysorbate 80, purified water, saccharin sodium, simethicone, and sodium citrate.

Diatrizoate meglumine is designated chemically as 1-deoxy-1-(methylamino)-D-glucitol 3,5-diacetamido-2,4,6-triiodo-benzoate (salt); diatrizoate sodium is monosodium 3, 5-diacetamido-2,4,6-triiodobenzoate. Structural formulas:

CLINICAL PHARMACOLOGY

The most important characteristic of contrast media is the iodine content. The relatively high atomic weight of iodine contributes sufficient radiodensity for radiographic contrast with surrounding tissues.

Diagnostic enteral radiopaque agents have few known pharmacological effects. Diatrizoate meglumine and diatrizoate sodium exert a mild laxative effect attributable to their high osmolarity.

Diatrizoate meglumine and diatrizoate sodium are sparingly absorbed from the intact gastrointestinal tract, and therefore permit gastrointestinal opacification and delineation after oral or rectal administration. Oral administration is used for radiographic evaluation of the esophagus, stomach and proximal small intestine. Rectal administration is used for examination of the colon; however, visualization of the distal small bowel is generally unsatisfactory, since the hypertonicity of the medium causes intraluminal diffusion of water with subsequent dilution of the medium. Enough absorption from the gastrointestinal tract to permit incidental visualization of the urinary tract has been reported; this should also be considered when thyroid testing is being contemplated, since iodine-mediated thyrotropic effects may occur (see PRECAUTIONS).

INDICATIONS AND USAGE

Gastrografin (Diatrizoate Meglumine and Diatrizoate Sodium Solution) is indicated for radiographic examination of segments of the gastrointestinal tract (esophagus, stomach, proximal small intestine, and colon). The preparation is particularly indicated when a more viscous agent such as barium sulfate, which is not water-soluble, is not feasible or is potentially dangerous.

Gastrografin may also be used as an adjunct to contrast enhancement in computed tomography of the torso (body imaging); the preparation is indicated, in conjunction with intravenous administration of a radiopaque contrast agent, when unenhanced imaging may not provide sufficient definition in distinguishing normal loops of bowel from adjacent organs or areas of suspected pathology.

CONTRAINDICATIONS

Do not administer to patients with a known hypersensitivity to Gastrografin or any of its components.

WARNINGS

Dehydration: Administration of hypertonic Gastrografin solutions may lead to hypovolemia and hypotension due to fluid loss from the intestine. A 1 in 4.6 (1:4.6) dilution of Gastrografin yields an approximately isotonic 16.5 percent diatrizoate salts solution; less dilute solutions are hypertonic and may lead to intraluminal movement of fluid with resulting hypovolemia. In young or debilitated children and in elderly cachectic persons, the loss of plasma fluid may be sufficient to cause a shock-like state. If Gastrografin is used in infants and children (under 10 kg) or in dehydrated or debilitated patients, the solution must be prepared using the specific dilutions described in DOSAGE AND ADMINISTRATION. In debilitated patients and in patients with electrolyte imbalances, postprocedural monitoring of hydration, serum osmolarity, electrolytes and clinical status is essential. In pediatric or severely debilitated patients, the maintenance of an open intravenous fluid line for rehydration may be advisable should hypotension or shock supervene. Electrolyte disturbances must be corrected prior to the administration of any hypertonic Gastrografin solutions.

Aspiration: Aspiration of Gastrografin into the trachea and airways may result in serious pulmonary complications including, pulmonary edema, pneumonitis or death Bronchial entry of any orally administered contrast medium causes a copious osmotic effusion. Therefore, avoid use of Gastrografin in patients with esophagotracheal fistula and minimize risks for pulmonary aspiration in all patients. If Gastrografin is given by nasogastric tube, the position of the tube in the stomach must be verified before administration.

Anaphylactic reactions: Anaphylactic reactions, including fatalities, have been reported with the use of Gastrografin. Patients at increased risk include those with a history of a previous reaction to a contrast medium, patients with a known sensitivity to iodine, and patients with a known clinical hypersensitivity (bronchial asthma, hay fever, and food allergies). Medical personnel trained in the treatment of anaphylactic reactions and the necessary drugs and medical equipment should always be readily available when Gastrografin is used.

PRECAUTIONS

General

Diagnostic procedures which involve the use of radiopaque contrast agents should be carried out under the direction of personnel with the prerequisite training and with a thorough knowledge of the particular procedure to be performed. Appropriate facilities should be available for coping with any complication of administration, as well as for treatment of reaction to the contrast medium (see ADVERSE REACTIONS, and PRECAUTIONS, Information for the Patient).

Rectal administration of undiluted Gastrografin (Diatrizoate Meglumine and Diatrizoate Sodium Solution) in any patient, particularly with large doses and/or in those with overdistention, has been reported to be associated with mucosal irritation.

Cases of hyperthyroidism have been reported with the use of oral contrast media. Some of these patients reportedly had multinodular goiters which may have been responsible for the increased hormone synthesis in response to excess iodine. Administration of an intravascular iodinated radiopaque diagnostic agent to a hyperthyroid patient precipitated thyroid storm; a similar situation could follow administration of oral preparations of iodides. Therefore, caution should be exercised when administering enteral gastrointestinal radiopaque agents to hyperthyroid and euthyroid goiterous patients.

Consideration should be given to the potential for precipitation of water-soluble contrast agents under conditions that may promote hyperacidity (i.e., fasting, emotional upset, or stress). Harmful effects directly attributable to precipitate formation have not been reported. However, the possibility of interpreting the precipitate radiologically as an anatomical abnormality (i.e., ulceration of the stomach or small intestine) or injury, should be kept in mind.

Information for the Patient

Patients should receive the following information and instructions:

1. This drug has been prescribed to perform an x-ray of the gastrointestinal tract.
2. Inform the physician if pregnant or if allergic to iodine, any foods, or x-ray materials.
3. The iodine in diatrizoate salts may interfere with some thyroid tests if these are needed in the future. Inform the attending physician at that time about this gastrointestinal study.
4. This drug may cause abdominal cramping, nausea, vomiting, diarrhea, skin rashes, itching, heartburn, dizziness, or headache in some patients, but most reactions are mild and pass quickly.

Drug/Laboratory Test Interactions

Thyroid Function Tests

The results of protein bound iodine (PBI) and radioactive iodine uptake studies, which depend on iodine estimations, will not accurately reflect thyroid function for six months, and possibly as long as one year, following the administration of diagnostic enteral radiopaque media.

Thyroid function tests, if indicated, generally should be performed prior to the administration of any iodinated agent. However, thyroid function can be evaluated after use of these agents by using T3 resin uptake and total or free thyroxine (T4) assays which are not dependent on iodine estimations.

Pancreatic Tests

Small quantities of contrast medium in the intestinal tract may cause false low trypsin values when determined spectrophotometrically. Therefore, duodenal instillation should not precede pancreatic function tests involving spectrophotometric trypsin assays.

Any test which might be affected by contrast media should be performed prior to administration of the contrast medium.

Carcinogenesis, Mutagenesis, Impairment of Fertility

Long-term studies in animals have not been performed to evaluate carcinogenic or mutagenic potential, or possible impairment of fertility in males or females.

Pregnancy

When administered intravenously, diatrizoate salts cross the placenta and are evenly distributed in fetal tissues.

No teratogenic effects attributable to diatrizoate meglumine or diatrizoate sodium have been observed in teratology studies performed in animals. There are, however, no adequate and well-controlled studies in pregnant women. Because small amounts of these agents may be absorbed, and animal teratology studies are not always predictive of human response, these agents should be used during pregnancy only when clearly needed.

Procedures including radiation involve a certain risk related to the exposure of the fetus.

Nursing Mothers

Diatrizoate meglumine is excreted in breast milk following intravascular administration.

Because small amounts of enteral gastrointestinal radiopaque agents may be absorbed following oral or rectal administration, caution should be exercised when they are administered to a nursing woman.

Pediatric Use

See WARNINGS, and PRECAUTIONS, General.

Local injury to the colonic mucosa, particularly in the presence of underlying disease which interferes with intestinal viability, has been reported in cases where recommended doses and dilutions (see DOSAGE AND ADMINISTRATION) were not used; when extemporaneous dosage is elected, the polysorbate 80 level in the dose may be a contributing factor to injury.

ADVERSE REACTIONS

Most adverse reactions to enteral diagnostic radiopaque agents are mild and transitory. Nausea, vomiting and/or diarrhea, urticaria with erythema, hypoxia, acute dyspnea, tachyarrhythmia, and anaphylaxis have occurred following ingestion of the contrast medium, particularly when high concentrations of large volumes of solution are administered. Severe changes in serum osmolarity and electrolyte concentrations may produce shock-like states (see WARNINGS). It should be kept in mind that serious or anaphylactoid reactions that may occur with intravascular administration of radiopaque contrast agents are theoretically possible following administration by other routes.

OVERDOSAGE

See WARNINGS regarding potential hypovolemia, hypotension, or shock. The maintenance of an open intravenous fluid line for rehydration may be advisable. See DOSAGE AND ADMINISTRATION for appropriate doses and dilutions. Treatment of an overdose should be directed toward the support of all vital functions, and prompt institution of symptomatic therapy.

DOSAGE AND ADMINISTRATION

General

This medium is not to be used for the preparation of solutions for parenteral administration. Oral or rectal administration only. Discard any unused portion after procedure.

The routine preparatory measures employed for barium studies are also appropriate for this agent.

For pediatric and severely cachectic patients the maintenance of an intravenous fluid line may be advisable.

Radiographic Examination of Segments of the Gastrointestinal Tract

Oral Administration: Adult oral dosage may range from 30 to 90 mL (11 to 33 g iodine), depending on the nature of the examination and the size of the patient. For infants and children less than 5 years of age, 30 mL (11 g iodine) are usually adequate; for children 5 to 10 years of age, the suggested dose is 60 mL (22 g iodine). These pediatric doses may be diluted 1:1, if desired, with water, carbonated beverage, milk, or mineral oil. When used in infants, the solution may be given in a nursing bottle. Pediatric doses may also be used in dehydrated and/or debilitated adult patients. A 1:1 dilution is also recommended when the contrast medium is used in elderly cachectic individuals.

For very young (under 10 kg) and debilitated children the dose should be diluted: 1 part Gastrografin (Diatrizoate Meglumine and Diatrizoate Sodium Solution) in 3 parts water is recommended.

For Enemas or Enterostomy Instillations: Gastrografin should be diluted when it is used for enemas and enterostomy instillations. When used as an enema, the suggested dilution for adults is 240 mL (88 g iodine) in 1,000 mL of tap water. For children under 5 years of age, a 1:5 dilution in tap water is suggested; for children over 5 years of age, 90 mL (33 g iodine) in 500 mL of tap water is a suitable dilution.

Tomography (Body Imaging)

A usual adult dose is 240 mL of a dilute Gastrografin solution prepared by diluting 25 mL (9.17 g iodine) to one liter with tap water. Less dilute solutions [up to 77 mL (28.26 g iodine) diluted to one liter with tap water] may be used when indicated. The dose is administered orally about 15 to 30 minutes prior to imaging in order to permit the contrast medium to reach the pelvic loops.

HOW SUPPLIED

Gastrografin (Diatrizoate Meglumine and Diatrizoate Sodium Solution USP) is available in packages of:
Twenty-four 30 mL single dose bottles (NDC 0270-0445-35).
Twelve 120 mL single dose bottles (NDC 0270-0445-40).

Storage

Protect from light. Store at 20-25°C (68-77°F) [See USP]; avoid excessive heat.

Manufactured by E-Z-EM Canada Inc,
Anjou, Quebec H1J2Z4, Canada
For Bracco Diagnostics Inc.
Monroe Township, NJ 08831

Rev. August 2019
CLE7903

Gastrografin® 120 mL Label
NDC 0270-0445-40

Gastrografin® 12 x 120 mL Bottles Label
NDC 0270–0445–40